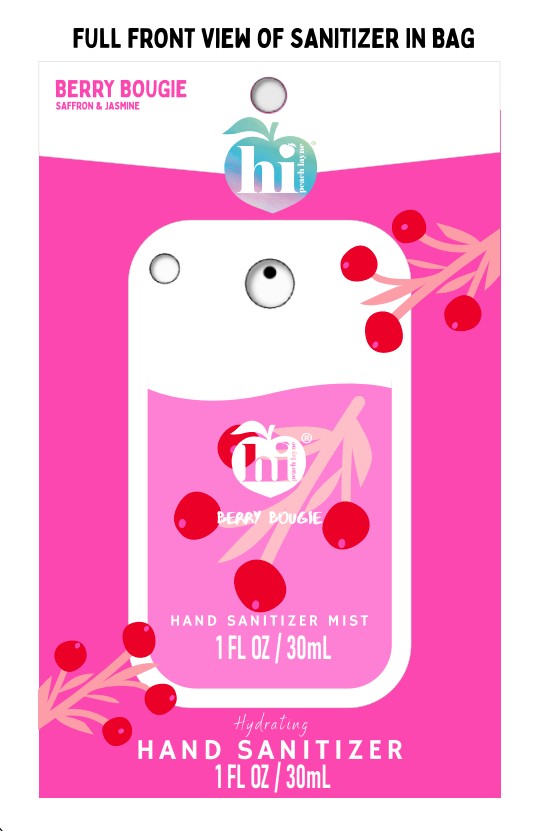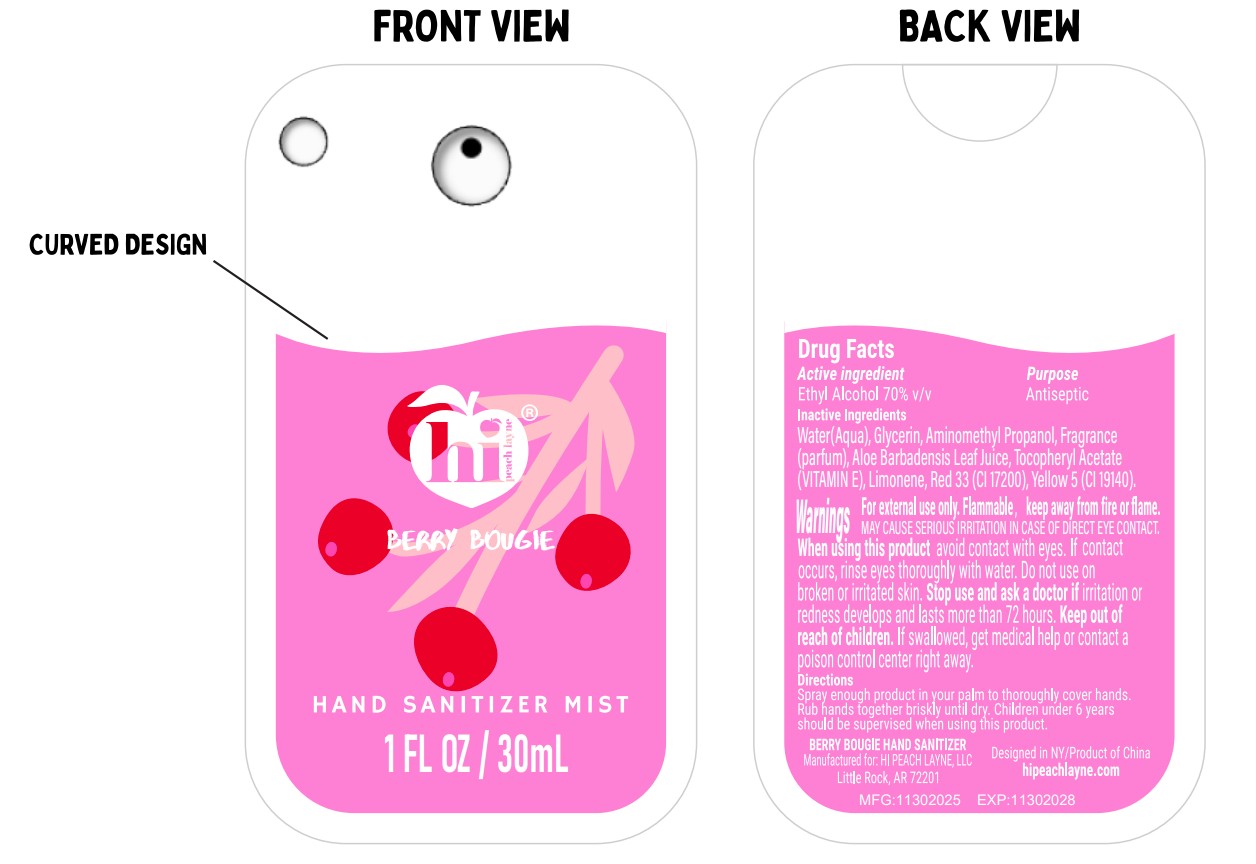 DRUG LABEL: hi peach layne
NDC: 73905-048 | Form: SPRAY
Manufacturer: Zhejiang Jinghui Cosmetics Share Co., Ltd.
Category: otc | Type: HUMAN OTC DRUG LABEL
Date: 20260115

ACTIVE INGREDIENTS: ALCOHOL 70 mL/100 mL
INACTIVE INGREDIENTS: YELLOW 5; GLYCERIN; WATER; LIMONENE, (+)-; ALPHA-TOCOPHEROL ACETATE; ALOE BARBADENSIS LEAF JUICE; RED 33; FRAGRANCE 13576; AMINOMETHYL PROPANOL

2-BERRY BOUGIE HAND SANITIZER-73905-048

ACTIVE INGREDIENT

Ethyl Alcohol 70% v/v

PURPOSE

Antiseptic

INACTIVE INGREDIENT

Water(Aqua),Glycerin,Aminomethyl Propanol, Fragrance(parfum), Aloe Barbadensis Leaf Juice, Tocopheryl Acetate(VITAMIN E),Limonene, Red 33 (CI 17200),Yellow 5(CI 19140)

WARNINGS

For external use only. Flammable, keep away from fire or flame.

MAY CAUSE SERIOUS IRRITATION IN CASE OF DIRECT EYE CONTACT.When using this product avoid contact with eyes. If contact occurs, rinse eyes thoroughly with water. Do not use on broken or irritated skin. Stop use and ask a doctor if irritation or redness develops and lasts more than 72 hours.

Keep out of reach of children.If swallowed,get medical help or contact a poison control center right away.

INDICATIONS AND USAGE

Spray enough product in your palm to thoroughly cover hands.Rub hands together briskly until dry. Children under 6 years should be supervised when using this product.

DOSAGE AND ADMINISTRATION

Spray enough product in your palm to thoroughly cover hands.Rub hands together briskly until dry.